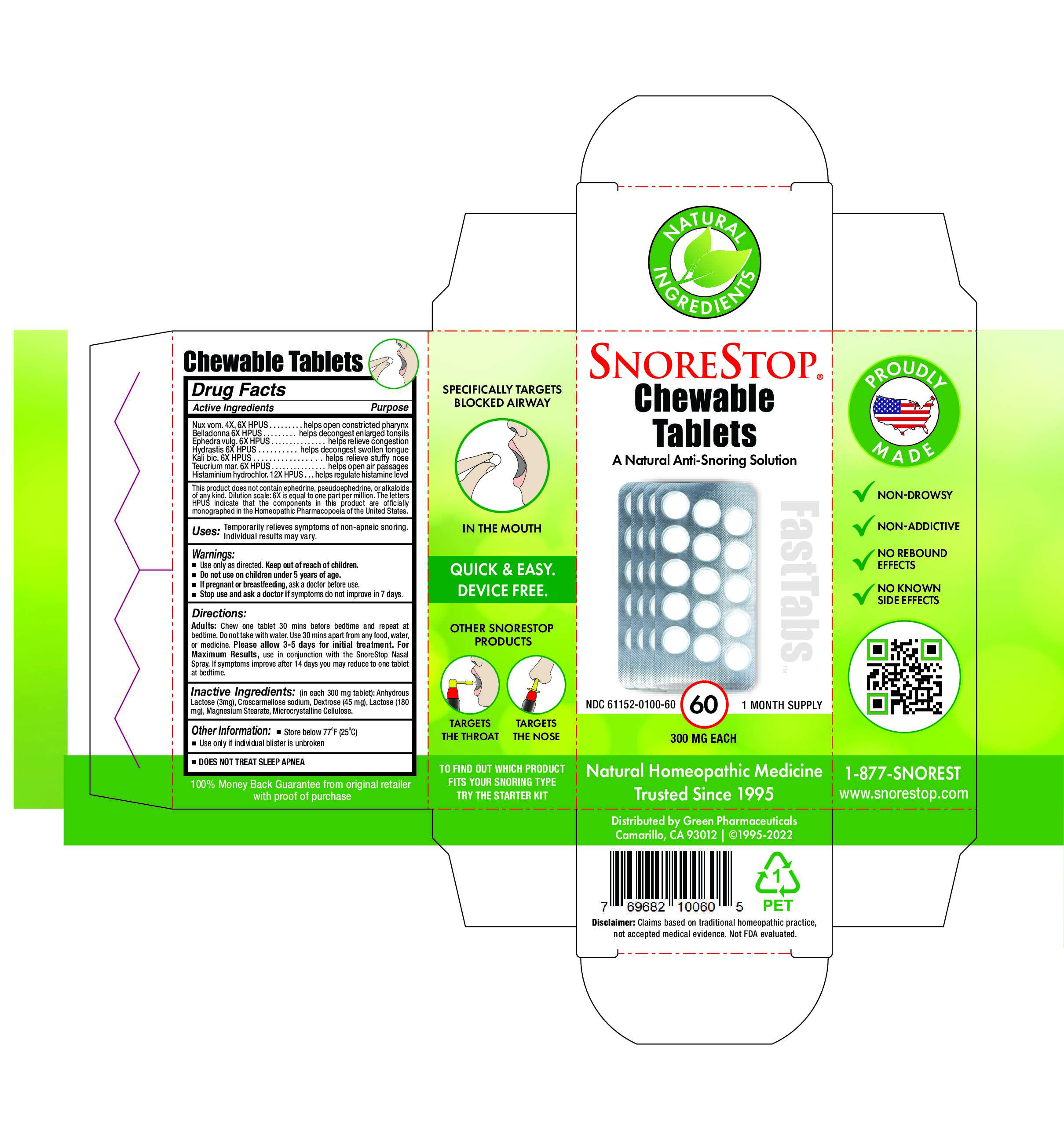 DRUG LABEL: SnoreStop Chewable Fast tabs 60
NDC: 61152-100 | Form: TABLET, CHEWABLE
Manufacturer: Green Pharmaceuticals Inc
Category: homeopathic | Type: HUMAN OTC DRUG LABEL
Date: 20250108

ACTIVE INGREDIENTS: ATROPA BELLADONNA 6 [hp_X]/30 1; EPHEDRA DISTACHYA FLOWERING TWIG 6 [hp_X]/30 1; HISTAMINE DIHYDROCHLORIDE 12 [hp_X]/30 1; GOLDENSEAL 6 [hp_X]/30 1; POTASSIUM DICHROMATE 6 [hp_X]/30 1; STRYCHNOS NUX-VOMICA SEED 6 [hp_X]/30 1; TEUCRIUM MARUM 6 [hp_X]/30 1
INACTIVE INGREDIENTS: ANHYDROUS LACTOSE; CROSCARMELLOSE SODIUM; DEXTROSE; LACTOSE; MAGNESIUM STEARATE; CELLULOSE, MICROCRYSTALLINE

SnoreStop Chewable Tablets 60

Ingredients (HPUS):

Belladonna 6X, Ephedra vulg. 6X, Histaminum hydrochlorinum 12X, Hydrastatis 6X, Kali bic. 6X, Nux vom. 4X, 6X, Teucrium mar. 6X.

Inactive Ingredients:

Anhydrous Lactose, Croscarmellose sodium, Dextrose (45mg/tab), Lactose (180mg/tab), Magnesium Stearate, Microcrystalline Cellulose.

Uses:

Temporarily relieves symptoms of non-apneic snoring. Individual results may vary.

Warnings:

Use only as directed. Keep out of reach of children. Do not use on children under 5 years of age. If pregnant or breastfeeding, ask a doctor before use. This product does not treat sleep apnea. Stop use and ask a doctor if symptoms do not improve in 7 days.

Indications & Usage:

Adults: Chew one tablet 30 mins before bedtime and repeat at bedtime. Do not take with water. Use 30 mins apart from any food, water, or medicine. Please allow 3-5 days for initial treatment. For Maximum Results, use in conjunction with the SnoreStop Nasal Spray. If symptoms improve after 14 days you may reduce to one tablet at bedtime.

Keep out of reach of children.

Other information:

Store below 77 °F (25 °C)
Use only if individual blister is unbroken
DOES NOT TREAT SLEEP APNEA

NON-DROWSY
NON-ADDICTIVE
NO REBOUND EFFECTS
NO KNOWN SIDE EFFECTS

Use only if individual blister is unbroken.

Questions?

1-877-SNOREST

Distributed by Green Pharmaceuticals
Camarillo, CA 93012 | ©1995-2002

Directions: Children over 5 years of age and Adults

Adults: Chew one tablet 30 mins before bedtime and repeat at bedtime. Do not take with water. Use 30 mins apart from any food, water, or medicine. Please allow 3-5 days for initial treatment. For Maximum Results, use in conjunction with the SnoreStop Nasal Spray. If symptoms improve after 14 days you may reduce to one tablet at bedtime.

Directions

Adults: Chew one tablet 30 mins before bedtime and repeat at bedtime. Do not take with water. Use 30 mins apart from any food, water, or medicine. Please allow 3-5 days for initial treatment. For Maximum Results, use in conjunction with the SnoreStop Nasal Spray. If symptoms improve after 14 days you may reduce to one tablet at bedtime.

Other Information

This product does not contain ephedrine, pseudoephedrine, or alkaloids of any kind. Dilution scale: 6X is equal to one part per million. The letters HPUS indicate that the components in this product are officially monographed in the Homeopathic Pharmacopeia of the United States.

Active Ingredients and purpose

Nux vom,4X,6X HPUS……………………………. helps open constricted pharynx
Belladonna 6X HPUS………………………………. helps decongest enlarged tonsils
Ephedra vulg. 6X HPUS……………………………helps relieve congestion
Hydrastis 6X, HPUS…………………………………helps decongest swollen tongue
Kali bic. 6X HPUS……………………………………. helps relieve stuffy nose
Teucrium mar. 6X HPUS…………………………. helps open air passages
Histaminium hydrochlor. 12X HPUS…………helps regulate histamine level

Description of Product

SnoreStop Chewable Tablets
A Natural Anti-Snoring Solution

NDC 61152-0100-60
60 1 MONTH SUPPLY